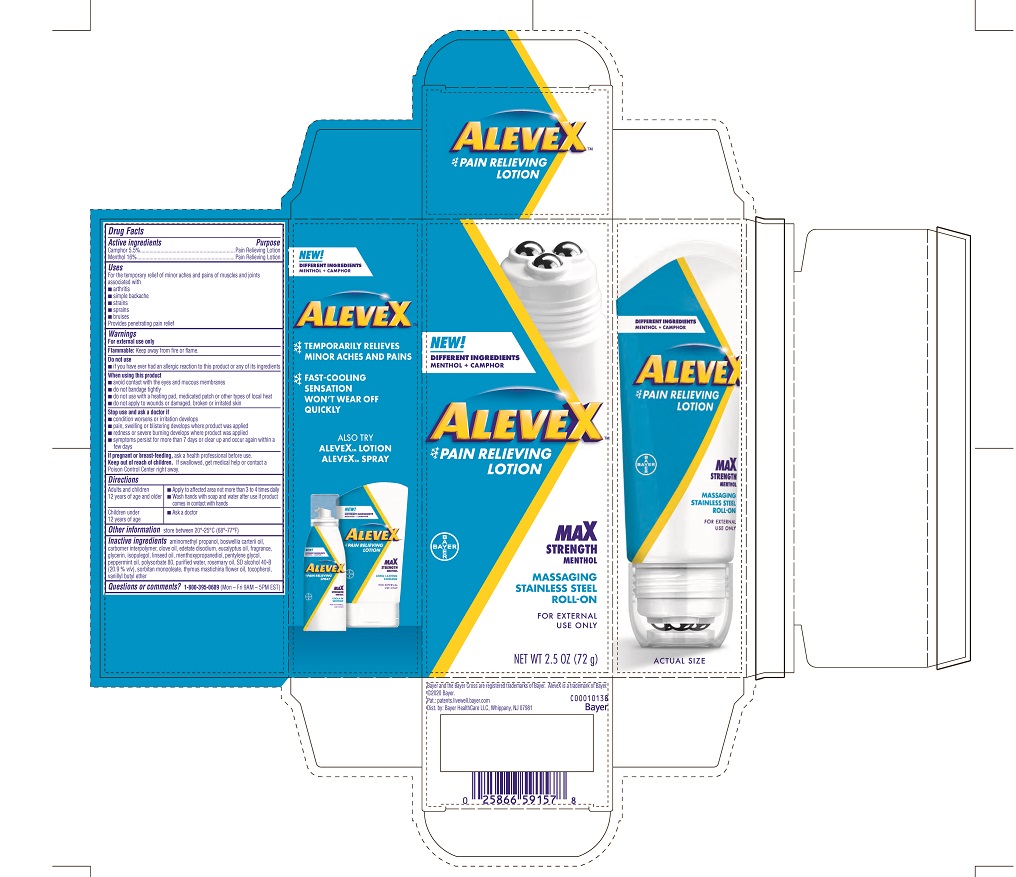 DRUG LABEL: AleveX
NDC: 0280-0050 | Form: LOTION
Manufacturer: Bayer HealthCare LLC
Category: otc | Type: HUMAN OTC DRUG LABEL
Date: 20251204

ACTIVE INGREDIENTS: MENTHOL 16 mg/1 g; CAMPHOR (SYNTHETIC) 5.5 mg/1 g
INACTIVE INGREDIENTS: PEPPERMINT OIL; LINSEED OIL; EDETATE DISODIUM; ALCOHOL; WATER; FRANKINCENSE OIL; ISOPULEGOL; CARBOMER INTERPOLYMER TYPE A (ALLYL SUCROSE CROSSLINKED); PENTYLENE GLYCOL; ROSEMARY OIL; THYMUS MASTICHINA FLOWERING TOP OIL; VANILLYL BUTYL ETHER; SORBITAN MONOOLEATE; 3-((L-MENTHYL)OXY)PROPANE-1,2-DIOL; EUCALYPTUS OIL; POLYSORBATE 80; AMINOMETHYLPROPANOL; TOCOPHEROL; CLOVE OIL; GLYCERIN

AleveX Lotion Rollerball UI 1614338

Drug Facts

Active ingredients
Camphor 5.5%
Menthol 16%

Purpose

Pain Relieving Lotion

Uses

For the temporary relief of minor aches and pains of muscles and joints associated with

- arthritis
- simple backache
- strains
- sprains
- bruises

Provides penetrating pain relief

Warnings

For external use only
Flammable: Keep away from fire or flame.

Do not use

- if you have ever had an allergic reaction to this product or any of its ingredients

When using this product

- avoid contact with the eyes and mucous membranes
- do not bandage tightly
- do not use with a heating pad, medicated patch or other types of local heat
- do not apply to wounds or damaged, broken or irritated skin

Stop use

- condition worsens or irritation develops
- pain, swelling or blistering develops where product was applied
- redness or severe burning develops where product was applied
- symptoms persist for more than 7 days or clear up and occur again within a few days

PREGNANCY OR BREAST FEEDING

If pregnant or breast-feeding, ask a healthcare professional before use.

Keep out of reach of children

If swallowed, get medical help or contact a Poison Control Center right away.

Directions

Adults and children 12 years of age and older | - Apply to affected area not more than 3 to 4 times daily - Wash hands with soap and water after use if product comes in contact with hands
Children under 12 years of age | - Ask a doctor

Other information

store between 20º-25ºC (68º-77ºF)

Inactive ingredients

aminomethyl propanol, boswellia carterii oil, carbomer interpolymer, clove oil, edetate disodium, eucalyptus oil, fragrance, glycerin, isopulegol, linseed oil, menthoxypropanediol, pentylene glycol, peppermint oil, polysorbate 80, purified water, rosemary oil, SD alcohol 40-B (20.9 % v/v), sorbitan monooleate, thymus mastichina flower, tocopherol, vanillyl butyl ether

Questions or comments?

1-800-395-0689 (Mon - Fri 9AM - 5PM EST)

AleveX Carton label 72 grams

NEW!
DIFFERENT INGREDIENTS
MENTHOL + CAMPHOR
ALEVEX™
PAIN RELIEVING
LOTION
MAX STRENGTH
MENTHOL
MASSAGING
STAINLESS
STEEL
ROLL-ON
FOR EXTERNAL
USE ONLY
NET WT 2.5 OZ. (72 g)